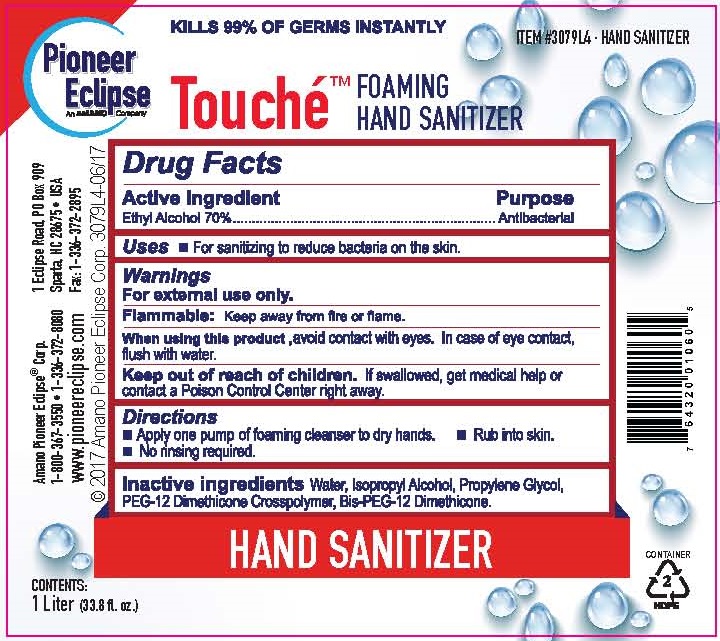 DRUG LABEL: PIONEER ECLIPSE TOUCHE FOAMING HAND SANITIZER
NDC: 70415-302 | Form: LIQUID
Manufacturer: CWGC LA Inc.
Category: otc | Type: HUMAN OTC DRUG LABEL
Date: 20230921

ACTIVE INGREDIENTS: ALCOHOL 70 mL/100 mL
INACTIVE INGREDIENTS: WATER; ISOPROPYL ALCOHOL; PROPYLENE GLYCOL; PEG-12 DIMETHICONE (300 CST); BIS-PEG-12 DIMETHICONE (70 MPA.S)

Pioneer Eclipse Touché Foaming Hand Sanitizer (70415-302)

Active ingredient

Ethyl Alcohol 70 %

PURPOSE

ANTIBACTERIAL

Uses

- For sanitizing to reduce bacteria on the skin.

Warnings

For external use only

Flammable :Keep away from fire or flame

WHEN USING

When using this productavoid contact with eyes. In case of eye contact, flush with water

Keep out of reach of children. If swallowed, get medical help or contact a Poison Control Center right away.

Directions

- Apply one pump of foaming cleanser to dry hands.
- Rub into skin.
- No rinsing required.

Inactive ingredients

Water, Isopropyl Alcohol, Propylene Glycol, PEG-12 Dimethicone Crosspolymer, BIS-PEG-12 Dimethicone.